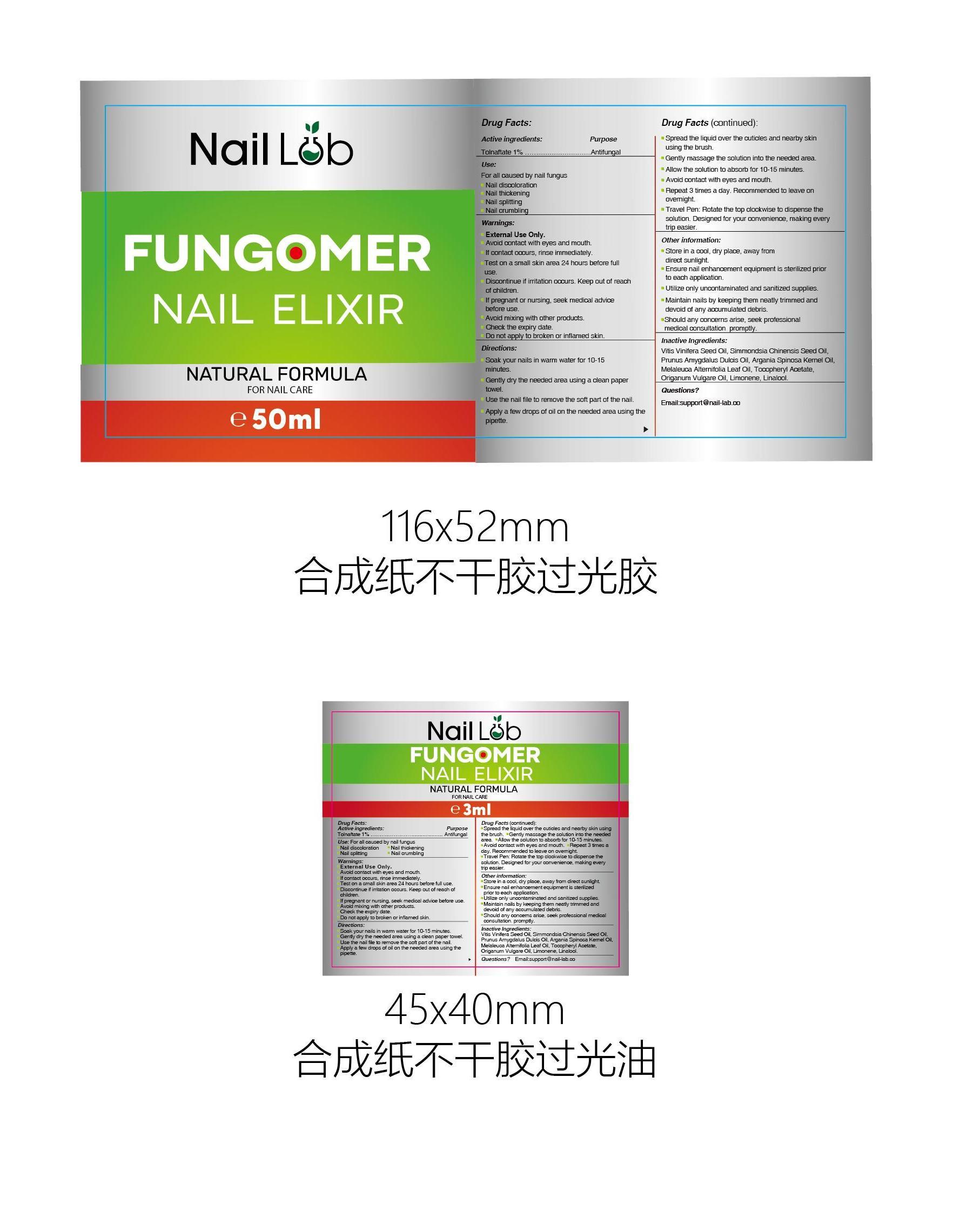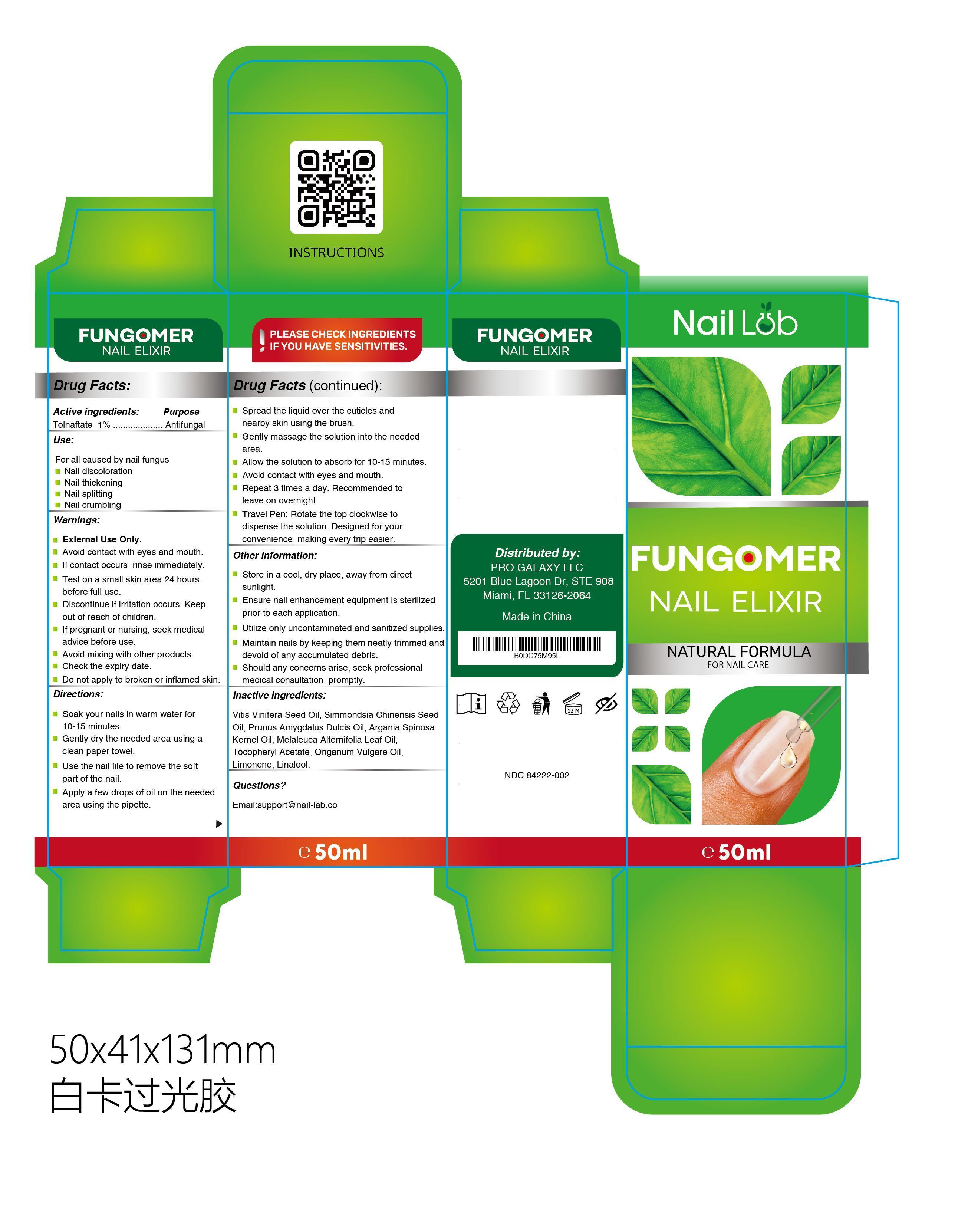 DRUG LABEL: NAIL LAB FUNGOMER NAILELIXIR
NDC: 84222-002 | Form: OIL
Manufacturer: Foshan Miwei Cosmetics Co., Ltd.
Category: otc | Type: HUMAN OTC DRUG LABEL
Date: 20250928

ACTIVE INGREDIENTS: TOLNAFTATE 1 g/100 mL
INACTIVE INGREDIENTS: LINALOOL 0.0015 mL/100 mL; ARGAN OIL 5 mL/100 mL; TEA TREE OIL 2.85 mL/100 mL; GRAPE SEED OIL 49.95 mL/100 mL; JOJOBA OIL 20 mL/100 mL; .ALPHA.-TOCOPHEROL ACETATE 1 mL/100 mL; ALMOND OIL 20 mL/100 mL; OREGANO LEAF OIL 1 mL/100 mL; LIMONENE, (+)- 0.15 mL/100 mL

NAIL LAB FUNGOMER NAIL ELIXIR

Active Ingredient

Tolnaftate 1%

Purpose

Antifungal

Uses

- For all caused by nail fungus
- Nail discoloration
- Nail thickening
- Nail splitting
- Nail crumbling

Warnings

- External Use Only.
- Avoid contact with eyes and mouth.
- If contact occurs, rinse immediately.
- Test on a small skin area 24 hours before full use.
- Discontinue if irritation occurs. Keep out of reach of children.
- If pregnant or nursing, seek medical advice before use.
- Avoid mixing with other products.
- Check the expiry date.
- Do not apply to broken or inflamed skin.

Do not apply to broken or inflamed skin.

WHEN USING

- Avoid contact with eyes and mouth.
- If contact occurs, rinse immediately.
- Test on a small skin area 24 hours before full use.

STOP USE

Discontinue if irritation occurs.

Keep out of reach of children.

PREGNANCY OR BREAST FEEDING

If pregnant or nursing, seek medical advice before use.

Directions:

- Soak your nails in warm water for 10-15 minutes.
- Gently dry the needed area using a clean paper towel.
- Use the nail file to remove the soft part of the nail.
- Apply a few drops of oil on the needed area using the pipette.
- Spread the liquid over the cuticles and nearby skin using the brush.
- Gently massage the solution into the needed area.
- Allow the solution to absorb for 10-1 5 minutes. Avoid contact with eyes and mouth.
- Repeat 3 times a day. Recommended to leave on overnight.
- Travel Pen: Rotate the top clockwise to dispense the solution. Designed for your convenience, making every trip easier.

STORAGE AND HANDLING

Store in a cool, dry place, away from direct sunlight.

Other information:

- Store in a cool, dry place, away from direct sunlight.
- Ensure nail enhancement equipment is sterilized prior to each application.
- Utilize only uncontaminated and sanitized supplies.
- Maintain nails by keeping them neatly trimmed and devoid of any accumulated debris.
- Should any concerns arise, seek professional medical consultation. promptly.

Inactive Ingredients:

Vitis Vinifera Seed Oil, Simmondsia Chinensis Seed Oil, Prunus Amygdalus Dulcis Oil, Argania Spinosa Kernel Oil, Melaleuca Alternifolia Leaf Oil, Tocopheryl Acetate, Origanum Vulgare Oil, Limonene, Linalool

Questions?

Email: support @ nail-lab.co